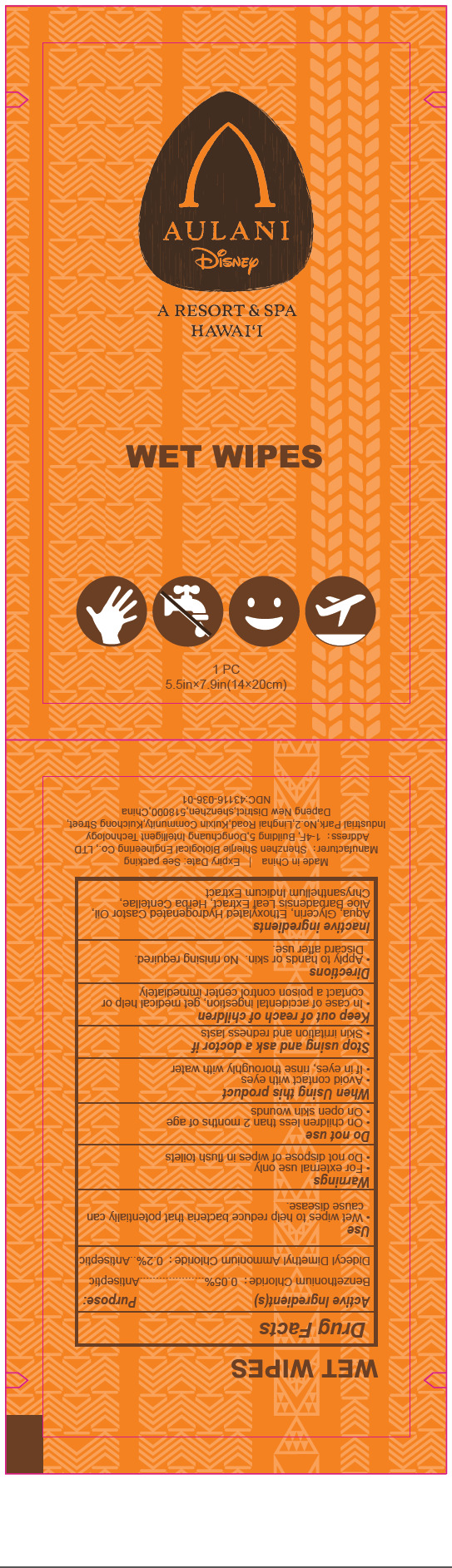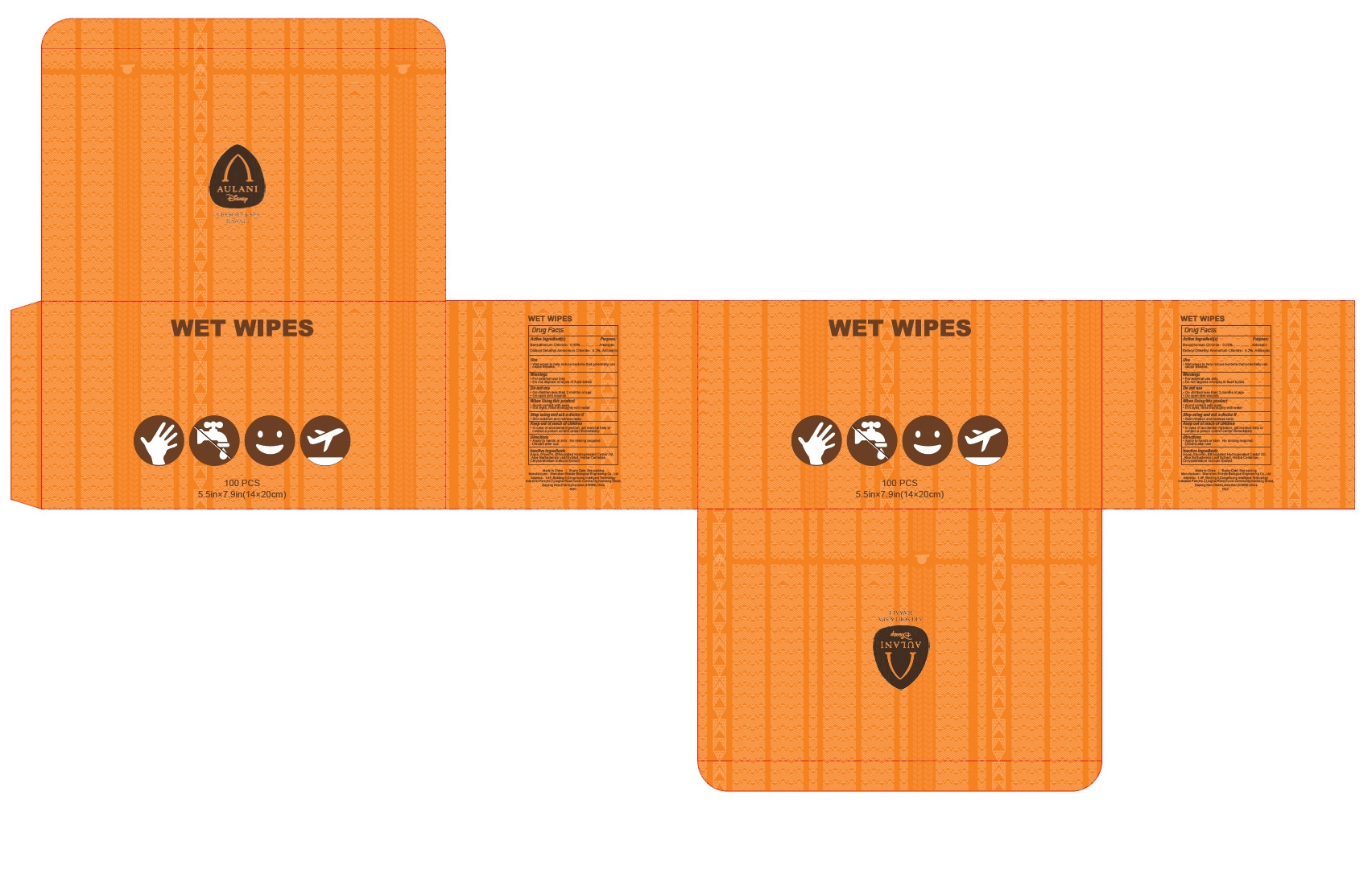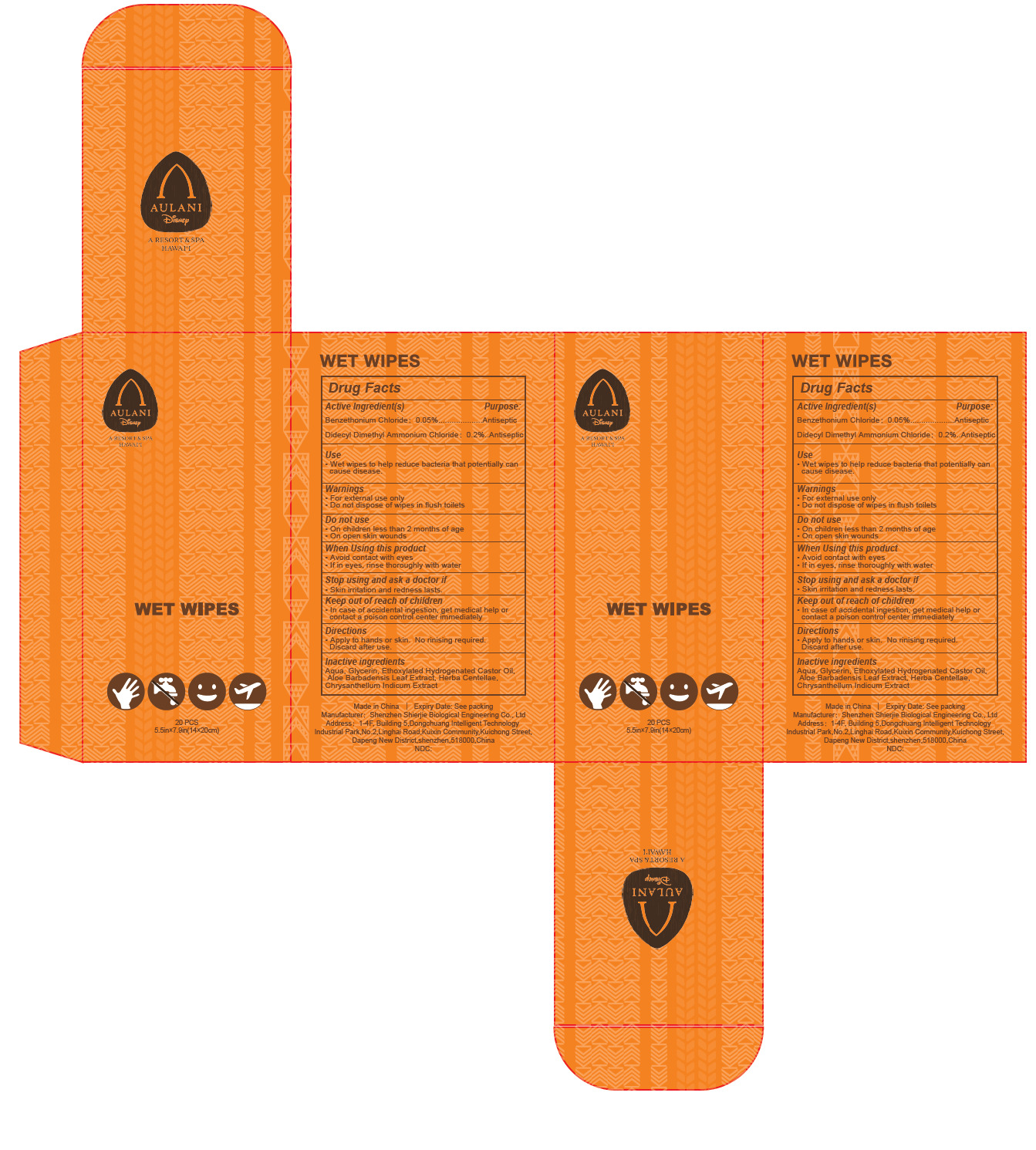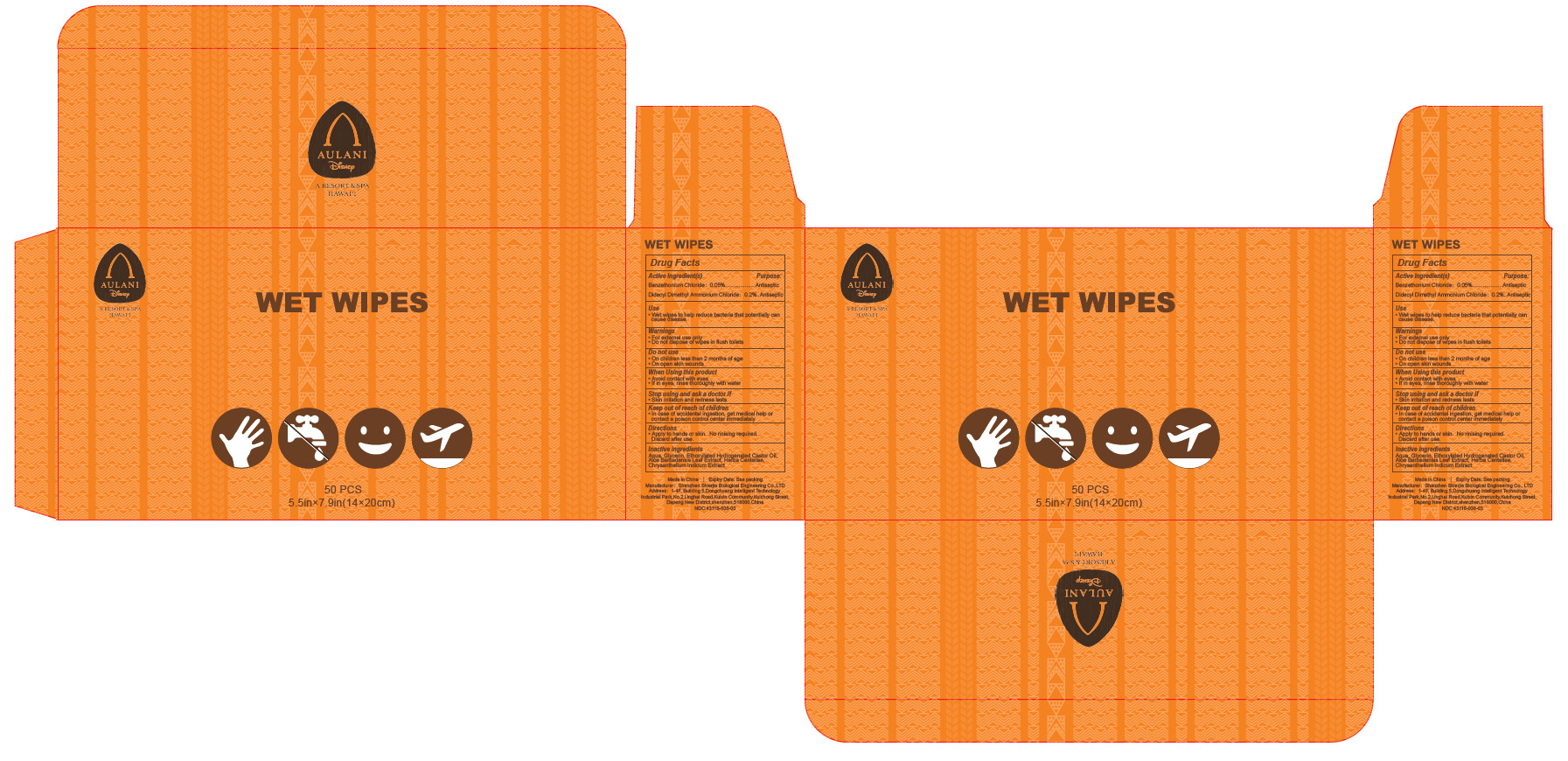 DRUG LABEL: Wet wipes
NDC: 43116-036 | Form: CLOTH
Manufacturer: Shenzhen Shierjie Biological Engineering Co., LTD
Category: otc | Type: HUMAN OTC DRUG LABEL
Date: 20260107

ACTIVE INGREDIENTS: DIDECYLDIMONIUM CHLORIDE 0.2 U/100 U; BENZETHONIUM CHLORIDE 0.05 U/100 U
INACTIVE INGREDIENTS: ALOE BARBADENSIS LEAF; POLYOXYL 40 HYDROGENATED CASTOR OIL; CENTELLA ASIATICA; AQUA; GLYCERIN; CHRYSANTHELLUM INDICUM TOP

43116-036

Active Ingredient

Benzethonium Chloride 0.05%

Didecyl Dimethyl Ammonium Chloride 0.2%

Purpose

Antiseptic

Use

Wet wipes to help reduce bacteria that potentially can cause disease.

Warnings

For external use only.

Do not dispose of wipes in flush toilets

Do not use

●On children less than 2 months of age
●On open skin wounds

When Using

Avoid contact with eyes
If in eyes, rinse thoroughly with water

Stop Use

Skin irritation and redness lasts.

Ask Doctor

If there is any discomfort during use, please stop using immediately.

Keep Oot Of Reach Of Children

In case of accidental ingestion, get medical help or contact a poison control center immediately

Directions

Apply to hands or skin. No rinising required. Discard after use.

Inactive ingredients

Aqua, Glycerin, Ethoxylated Hydrogenated Castor Oil, Aloe Barbadensis Leaf Extract, Herba Centellae,
Chrysanthellum Indicum Extract